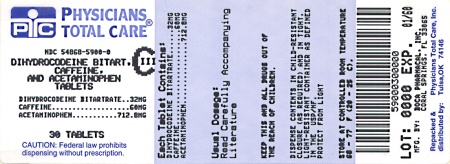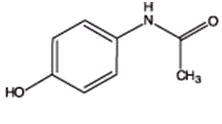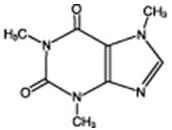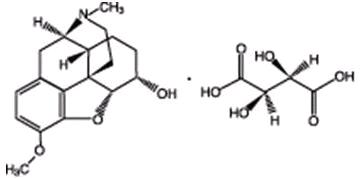 DRUG LABEL: Dihydrocodeine Bitartrate, Acetaminophen and Caffeine
NDC: 54868-5900 | Form: TABLET
Manufacturer: Physicians Total Care, Inc.
Category: prescription | Type: HUMAN PRESCRIPTION DRUG LABEL
Date: 20091124
DEA Schedule: CIII

ACTIVE INGREDIENTS: DIHYDROCODEINE BITARTRATE 32 mg/1 1; ACETAMINOPHEN 712.8 mg/1 1; CAFFEINE 60 mg/1 1
INACTIVE INGREDIENTS: CROSPOVIDONE; MAGNESIUM STEARATE; CELLULOSE, MICROCRYSTALLINE; POVIDONE; STARCH, CORN; STEARIC ACID

Acetaminophen, Caffeine and Dihydrocodeine Bitartrate Tablets

DESCRIPTION

Acetaminophen, caffeine, and dihydrocodeine bitartrate tablets are supplied in tablet form for oral administration.

Each tablet contains:
Acetaminophenִִִִִִִִִִִִִִִִִִִִִִִִִִִִִִִִ712.8 mg
Caffeineִִִִִִִִִִִִִִִִִִִִִִִִִִִִִִִִִִִִִִִִִִִִִ60 mg
Dihydrocodeine* bitartrateִִִִִִִִִִִִִִִִִִִִִִ32 mg
*Warning: May be habit forming

Acetaminophen (4'-hydroxyacetanilide), a slightly bitter, white, odorless, crystalline powder, is a non-opiate, non-salicylate analgesic and antipyretic.

It has the following structural formula:

C8H9NO2 M.W.=151.16

Caffeine (1,3,7-trimethylxanthine), a bitter, white crystalline powder, is a central nervous system stimulant. It has the following structural formula:

C8H10N4O2 M.W=194.19

Dihydrocodeine Bitartrate (4,5a-epoxy-3-methoxy-17-methylmDihydrocodeine Bitartrate (4,5a-epoxy-3-methoxy-17-methylmDihydrocodeine Bitartrate (4,5a-epoxy-3-methoxy-17-methylmDihydrocodeine Bitartrate (4,5a-epoxy-3-methoxy-17-methylmorphinan-6a-ol (+)-tartrate), an odorless, fine white powder is an opioid analgesic. It has the following structural formula:

C18H23NO3 C4H6O6 M.W.=451.47

In addition, each tablet also contains the following inactive ingredients: crospovidone, magnesium stearate, microcrystalline cellulose, povidone, pregelatinized starch, stearic acid.

CLINICAL PHARMACOLOGY:

Acetaminophen, caffeine, and dihydrocodeine bitartrate tablets contain dihydrocodeine which is a semisynthetic narcotic analgesic related to codeine, with multiple actions qualitatively similar to those of codeine; the most prominent of these involve the central nervous system and organs with smooth muscle components. The principal action of therapeutic value is analgesia.

This combination product also contains acetaminophen, a non-opiate, non-salicylate analgesic and antipyretic. This combination product contains caffeine as an analgesic adjuvant. Caffeine is also a central nervous system and cardiovascular stimulant.

INDICATIONS AND USAGE:

Acetaminophen, caffeine, and dihydrocodeine bitartrate tablets are indicated for the relief of moderate to moderately severe pain.

CONTRAINDICATIONS:

This combination product is contraindicated in persons with hypersensitivity to dihydrocodeine, codeine, acetaminophen, caffeine, or any of the inactive components listed above, or any situation where opioids are contraindicated including significant respiratory depression (in unmonitored settings or in the absence of resuscitative equipment), acute or severe bronchial asthma or hypercapnia, and paralytic ileus.

WARNINGS:

Usage in Ambulatory Patients:

Dihydrocodeine may impair the mental and/or physical abilities required for the performance of potentially hazardous tasks such as driving a car or operating machinery.

Respiratory Depression:

Respiratory depression is the most dangerous acute reaction produced by opioid agonist preparations, although it is rarely severe with usual doses. Opioids decrease the respiratory rate, tidal volume, minute ventilation, and sensitivity to carbon dioxide. Respiratory depression occurs most frequently in elderly or debilitated patients, usually after large initial doses in nontolerant patients, or when opioids are given in conjunction with other agents that depress respiration. This combination product should be used with caution in patients with significant chronic obstructive pulmonary disease or corpulmonale and in patients with a substantially decreased respiratory reserve, hypoxia, hypercapnia, or respiratory depression. In such patients, alternative non-opioid analgesics should be considered, and opioids should be admin- istered only under careful medical supervision at the lowest effective dose.

Head Injury:

This combination product should be used cautiously in the presence of head injury or increased intracranial pressure. The effects of opioids on pupillary response and consciousness may obscure neurologic signs of increases in intracranial pressure in patients with head injuries. The respiratory depressant effects including carbon dioxide retention and secondary elevation of cerebrospinal fluid pressure may be markedly exaggerated in the presence of head injury, intracranial lesions, or other causes of increased intracranial pressures.

Hypotensive Effect:

Dihydrocodeine, like all opioid analgesics, may cause hypotension in patients whose ability to maintain blood pressure has been compromised by a depleted blood volume or who receive concurrent therapy with drugs such as phenothiazines or other agents which compromise vasomotor tone.

Acetaminophen, caffeine, and dihydrocodeine bitartrate tablets may produce orthostatic hypotension in ambulatory patients. This combination product should be administered with caution to patients in circulatory shock, since vasodilation produced by the drug may further reduce cardiac output and blood pressure.

Drug Dependence

Dihydrocodeine can produce drug dependence of the codeine type and has the potential of being abused (See DRUG ABUSE AND DEPENDENCE).

PRECAUTIONS:

General:

Selection of patients for treatment with Acetaminophen, caffeine, and dihydrocodeine bitartrate tablets should be governed by the same principles that apply to the use of similar opioid/non-opioid fixed combination analgesics. As with any such opioid analgesic, the dosing regimen should be adjusted for each patient (see DOSAGE AND ADMINISTRATION). This combination product should be used with caution in elderly or debilitated patients or those with any of the following conditions: acute alcoholism; adrenocortical insufficiency (e.g., Addison's disease); asthma; central nervous system depression or coma; chronic obstructive pulmonary disease; decreased respiratory reserve (including emphysema, severe obesity, cor pulmonale, or kyphoscoliosis); delirium tremens; head injury; hypotension; increased intracranial pressure; myxedema or hypothyroidism; prostatic hypertrophy or urethral stricture; and toxic psychosis. The benefits and risks of using opioids in patients taking monoamine oxidase inhibitors and in those with a history of drug abuse should be carefully considered. The administration of an analgesic containing an opioid may obscure the diagnosis or clinical course in patients with acute abdominal conditions. This combination product may aggravate convulsions in patients with convulsive disorders and, like all opioids, may induce or aggravate seizures in some clinical settings. Acetaminophen is relatively non-toxic at therapeutic doses, but should be used with caution in patients with severe renal or hepatic disease. Care should be observed when using large doses of acetaminophen in malnourished patients or those with a history of chronic alcohol abuse because they may be more susceptible to hepatic damage similar to that observed with toxic overdosage.

Caffeine in high doses may produce central nervous system and cardiovascular stimulation and gastrointestinal irritation.

Drug-Drug Interactions:

Dihydrocodeine with Other Central Nervous System Depressants:

Patients receiving other opioid analgesics, sedatives or hypnotics, muscle relaxants, general anesthetics, centrally acting anti-emetics, phenothiazines or other tranquilizers, or alcohol concomitantly with this combination product may exhibit additive depressant effects on the central nervous system. When such combined therapy is contemplated, the dose of one or both agents should be reduced.

Dihydrocodeine with Monoamine Oxidase Inhibitors:

Dihydrocodeine, like all opioid analgesics, interacts with monoamine oxidase inhibitors causing central nervous system excitation and hypertension.

Dihydrocodeine with Mixed Agonist/Antagonist Opioid Analgesics:

Agonist/antagonist analgesics (i.e., pentazocine, nalbuphine, butorphanol and buprenorphine) may reduce the analgesic effect of this combination product.

Acetaminophen-Drug Interactions:

Chronic and excessive consumption of alcohol may increase the hepatotoxic risk of acetaminophen. The potential for hepatotoxicity with acetaminophen also may be increased in patients receiving anticonvulsants that induce hepatic microsomal enzymes (including phenytoin, barbiturates, and carbamazepine) or isoniazide. Chronic ingestion of large doses of acetaminophen may slightly potentiate the effects of warfarin- and indandione- derivative anticoagulants. Severe hypothermia is possible in patients receiving acetaminophen concomitantly with phenothiazines.

Caffeine-Drug Interactions:

Caffeine may enhance the cardiac inotropic effects of beta-adrenergic stimulating agents. Coadministration of caffeine and disulfiram may lead to a substantial decrease in caffeine clearance. Caffeine may increase the metabolism of other drugs such as phenobarbital and aspirin. Caffeine accumulation may occur when products or foods containing caffeine are consumed concomitantly with quinolones such as ciprofloxacin.

Information for Patients/Caregivers:

Patients receiving Acetaminophen, caffeine, and dihydrocodeine bitartrate tablets should be given the following information:

1. Patients should be advised that Acetaminophen, caffeine and dihydrocodeine bitartrate tablet may impair the mental or physical abilities required for the performance of potentially hazardous tasks such as driving a car or operating machinery.
2. Patients should be advised to report adverse experiences occurring during therapy.
3. Patients should be advised not to adjust the dose of Acetaminophen, caffeine and dihydrocodeine bitartrate tablet without consulting the prescribing professional.
4. Patients should not combine Acetaminophen, caffeine and dihydrocodeine bitartrate tablet with alcohol or other central nervous system depressants (sleep aids, tranquilizers) except by the orders of the prescribing physician, because additive effects may occur.
5. Women of childbearing potential who become, or are planning to become, pregnant should be advised to consult their physician regarding the effects of analgesics and other drug use during pregnancy on themselves and their unborn child.
6. Patients should be advised that Acetaminophen, caffeine, and dihydrocodeine bitartrate tablets are a potential drug of abuse. They should protect it from theft, and it should never be given to anyone other than the individual for whom it was prescribed.

Pregnancy:

Teratogenic Effects – Pregnancy Category C.

Animal reproduction studies have not been conducted with Acetaminophen, caffeine, and dihydrocodeine bitartrate tablets. It is also not known whether this combination product can cause fetal harm when administered to pregnant women or can affect reproduction capacity in males and females. This combination product should be given to pregnant women only if clearly needed, especially during the first trimester.

Labor and Delivery:

Acetaminophen, caffeine, and dihydrocodeine bitartrate tablets are not recommended for use by women during and immediately before labor and delivery because oral opioids may cause respiratory depression in the newborn.

Nursing Mothers:

Dihydrocodeine bitartrate, acetaminophen and caffeine tablets are excreted in breast milk in small amounts, but the significance of their effects on nursing infants is not known. Because of the potential for serious adverse reactions in nursing infants from this combination product, a decision should be made whether to discontinue nursing or to discontinue the drug, taking into account the importance of the drug to the mother.

Pediatric Use:

Safety and effectiveness of Acetaminophen, caffeine, and dihydrocodeine bitartrate tablets in pediatric patients have not been established.

Geriatric Use:

Acetaminophen, caffeine, and dihydrocodeine bitartrate tablets should be given with caution to the elderly.

Hepatic Impairment:

Acetaminophen, caffeine, and dihydrocodeine bitartrate tablets should be given with caution to patients with hepatic insufficiency. Since dihydrocodeine is metabolized by the liver and since acetaminophen potentially causes hepatotoxicity, the effects of this combination product should be monitored closely in such patients.

Renal Impairment:

Acetaminophen, caffeine, and dihydrocodeine bitartrate tablets should be used with caution and at reduced dosage in the presence of impaired renal function.

Pancreatic/Biliary Tract Disease:

Opioids may cause spasms of the sphincter of Oddi and should be used with caution in patients with biliary tract disease including pancreatitis.

ADVERSE REACTIONS:

Dihydrocodeine:

The most frequently observed adverse reactions include light-headedness, dizziness, drowsiness, headache, fatigue, sedation, sweating, nausea, vomiting, constipation, pruritus, and skin reactions. With the exception of constipation, tolerance develops to most of these effects. Other reactions that have been observed with dihydrocodeine or other opioids include respiratory depression, orthostatic hypotension, cough suppression, confusion, diarrhea, miosis, abdominal pain, dry mouth, indigestion, anorexia, spasm of biliary tract, and urinary retention. Physical and psychological dependence are possibilities. Hypersensitivity reactions (including anaphylactoid reactions), hallucinations, vivid dreams, granulomatous interstitial nephritis, severe narcosis and acute renal failure have been reported rarely during dihydrocodeine administration.

Acetaminophen:

Acetaminophen in therapeutic doses rarely causes adverse reactions.

The most serious adverse reaction is hepatoxicity from overdosage (see OVERDOSAGE). Thrombocytopenia, leukopenia, pancytopenia, neutropenia, thrombocytopenic purpura, and agranulocytosis have been reported in patients receiving acetaminophen or p-aminophenol derivatives. Hypersensitivity reactions including urticarial or erythematous skin reactions, laryngeal edema, angioedema, or anaphylactoid reactions are rare.

Caffeine:

Adverse reactions associated with caffeine use include anxiety, anxiety neurosis, excitement, headaches, insomnia, irritability, lightheadedness, restlessness, tenseness, tremor, extrasystoles, palpitations, tachycardia, diarrhea, nausea, stomach pain, vomiting, diuresis, urticarcia, scintillating scotoma, and tinnitus.

DRUG ABUSE AND DEPENDENCE:

This combination product is subject to the provisions of the Controlled Substance Act, and has been placed in Schedule III.

Dihydrocodeine can produce drug dependence of the codeine type and therefore has the potential of being abused.

Like other opioid analgesics, dihydrocodeine may produce subjective effects other than analgesia (e.g., euphoria, relaxation), which may contribute to abuse by some patients. Psychological dependence, physical dependence, and tolerance may develop upon repeated administration of dihydrocodeine, and It should be prescribed and administered with the same degree of caution appropriate to the use of other oral opioid analgesic medications.

Symptoms of dihydrocodeine withdrawal consist of irritability, restlessness, insomnia, diaphoresis, anxiety and palpitations.

Prolonged, high intake of caffeine may produce tolerance and habituation. Physical signs of withdrawal, such as headaches, irritation, nervousness, anxiety, and dizziness may occur upon abrupt discontinuation.

OVERDOSAGE:

Following an acute overdosage with Acetaminophen, caffeine, and dihydrocodeine bitartrate tablets, toxicity may result from the dihydrocodeine, acetaminophen, or, less likely, caffeine component. An overdose is a potentially lethal polydrug overdose situation, and consultation with a regional poison control center is recommended. A listing of the poison control centers can be found in standard references such as the Physician's Desk Reference®.

Signs and Symptoms and Laboratory Findings:

Toxicity from dihydrocodeine is typical of opioids and includes pinpoint pupils, respiratory depression, and loss of consciousness. Convulsions, cardiovascular collapse, and death may occur. A single case of acute rhabdomyolysis associated with an overdose of dihydrocodeine has been reported. With acetaminophen, dose-dependent potentially fatal hepatic necrosis is the most serious adverse effect. Renal tubular necrosis, hypoglycemic coma, and thrombocytopenia may occur. Early symptoms of hepatotoxicity include nausea, vomiting, diaphoresis, and general malaise. Clinical and laboratory evidence of hepatic toxicity may not be apparent until 48 to 72 hours after ingestion. Acute caffeine poisoning may cause insomnia, restlessness, tremor, delirium, tachycardia, extrasystoles, and seizures.

Because overdose information on this combination product is limited, it is unclear which of the signs and symptoms of toxicity would manifest in any particular overdose situation.

Treatment:

Immediate treatment of an overdosage of Acetaminophen, caffeine, and dihydrocodeine bitartrate tablets includes support of cardiorespiratory function and measures to reduce drug absorption. Vomiting should be induced with syrup of ipecac, if the patient is alert and has adequate laryngeal reflexes. Oral activated charcoal should follow. The first dose of charcoal should be accompanied by an appropriate cathartic. Gastric lavage may be necessary. Hypotension is usually hypovolemic and should be treated with fluids. Endotracheal intubation and artificial respiration may be necessary. Peritoneal or hemodialysis may be necessary. If hypoprothrombinemia occurs, Vitamin K should be administered.

A pure opioid antagonist, such as naloxone or nalmefene, is a specific antidote against respiratory depression which results from opioid overdose. Opioid antagonists should not be given in the absence of clinically significant respiratory or circulatory depression secondary to opioid overdose. They should be administered cautiously to persons who are known, or suspected to be, physically dependent on any opioid agonist including Acetaminophen, caffeine, and dihydrocodeine bitartrate tablets. In such cases, an abrupt or complete reversal of opioid effects may precipitate an acute abstinence syndrome. The prescribing information for the specific opioid antagonist should be consulted for details of their proper use.

In adults and adolescents, regardless of the quantity of acetaminophen reported to have been ingested, acetylcysteine should be administered immediately if 24 hours or less have elapsed from the reported time of ingestion. It is not advisable to await the plasma concentration determination of acetaminophen before administering acetylcysteine. Serum liver enzyme levels should be measured. Therapy in children involves a similar treatment scheme; however, a regional Poison Control Center should be contacted. No specific antidote is available for caffeine. In addition to the supportive measures above, administration of demulcents such as aluminum hydroxide gel may diminish gastrointestinal irritation. Seizures may be treated with intravenous diazepam or a barbiturate.

DOSAGE AND ADMINISTRATION

The usual adult dosage is one (1) Acetaminophen, caffeine, and dihydrocodeine bitartrate tablets orally every four (4) hours, as needed. Dosage should be adjusted according to the severity of the pain and the response of the patient. No more than one (1) tablet should be taken in a 4-hour period. No more than five (5) doses, or five (5) tablets should be taken in a 24-hour period.

HOW SUPPLIED:

Acetaminophen, caffeine, and dihydrocodeine bitartrate tablets, containing acetaminophen 712.8 mg, caffeine 60 mg and dihydrocodeine* bitartrate 32 mg (*Warning: May be habit-forming). Tablets are white, oval-shaped single scored and are debossed “Boca” on one side and “611” on the other side; are supplied in

Bottles of 30 | NDC 54868-5900-0

Store at 20°C to 25°C (68°F to 77°F). [see USP Controlled Room Temperature]. Protect from moisture.

Dispense in a tight, light-resistant container with a child-resistant closure.

Call your doctor for medical advice about side effects. You may report side effects to the FDA at 1-800-FDA-1088.

Rx Only

Manufactured for:
Boca Pharmacal, Inc.
Coral Springs, FL 33065
www.bocapharmacal.com

Rev. 06/09

Physician’s Desk Reference® is the registered trademark of Thomson Healthcare, Inc.

Relabeling and Repackaging by:
Physicians Total Care, Inc.
Tulsa, OK 74146

PACKAGE LABEL.PRINCIPAL DISPLAY PANEL

Dihydrocodeine/Acetaminophen/Caffeine

32 mg/712.8 mg/60 mg